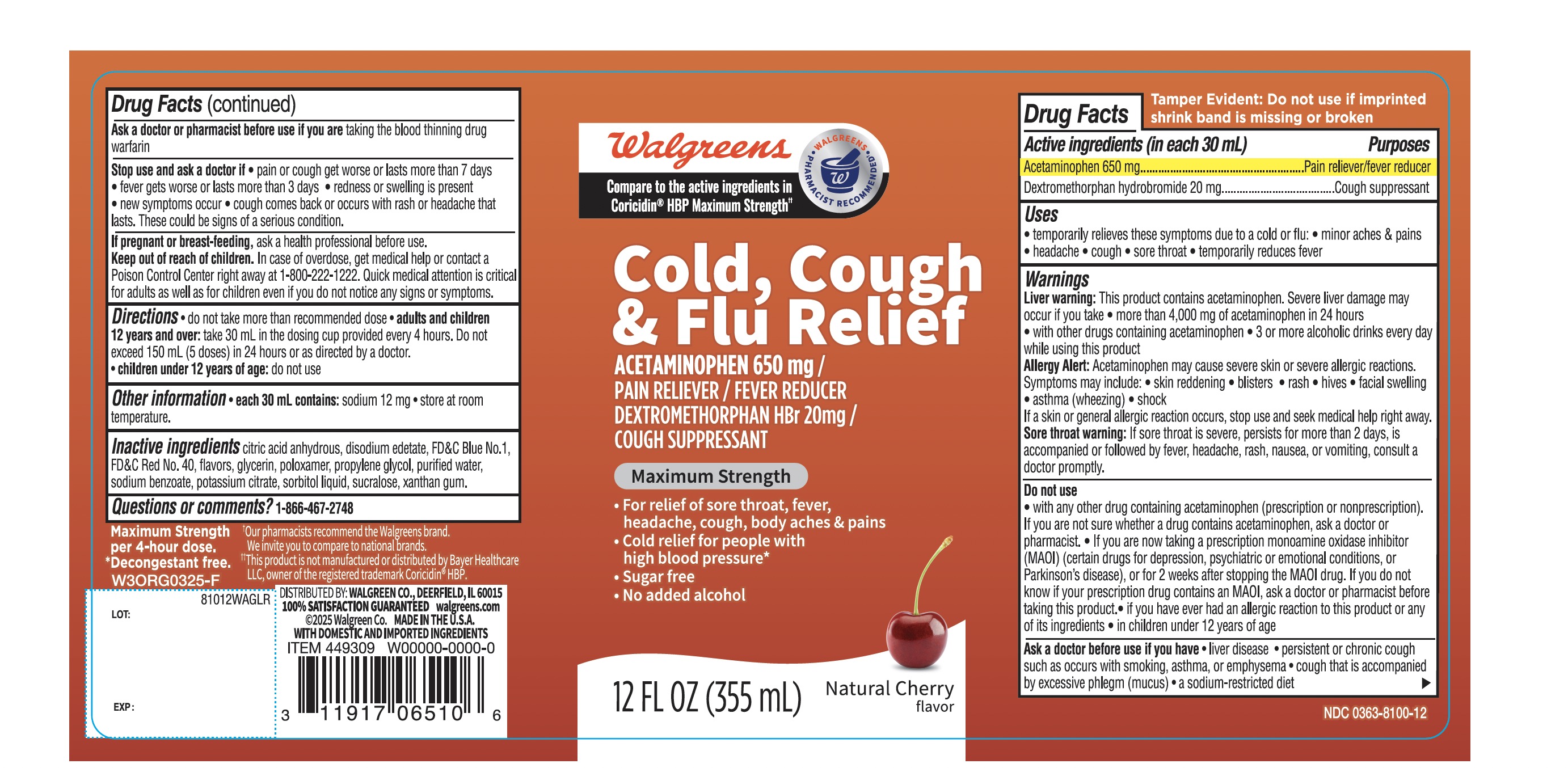 DRUG LABEL: WALGREENS

NDC: 0363-8100 | Form: LIQUID
Manufacturer: WALGREENS CO.
Category: otc | Type: HUMAN OTC DRUG LABEL
Date: 20251201

ACTIVE INGREDIENTS: ACETAMINOPHEN 650 mg/30 mL; DEXTROMETHORPHAN HYDROBROMIDE 20 mg/30 mL
INACTIVE INGREDIENTS: ANHYDROUS CITRIC ACID; EDETATE DISODIUM; FD&C BLUE NO. 1; FD&C RED NO. 40; GLYCERIN; POLOXAMER 105; PROPYLENE GLYCOL; WATER; SODIUM BENZOATE; POTASSIUM CITRATE; SORBITOL; SUCRALOSE; XANTHAN GUM

Walgreen Cold , Cough & FluRelief

Active Ingredients (in each 30 mL)

Acetaminophen 650 mg

Dextromethorphan HBr 20 mg

Purpose

Pain reliever/fever reducer

Cough Suppressant

Uses

- temporarily relieves these symptoms due to a cold or flu:
  - minor aches and pains
  - headache
  - cough
  - sore throat
- temporarily reduces fever

Warnings
Liver warning:This product contains acetaminophen. Severe liver damage may occur if you take
• more than 4,000 mg of acetaminophen in 24 hours
• with other drugs containing acetaminophen
• 3 or more alcoholic drinks every day while using this product

Allergy alert:Acetaminophen may cause severe skin or severe allergic reactions. Symptoms may include:

- skin reddening
- blisters
- rash
- hives
- facial swelling
- asthma (wheezing)
- shock

If a skin or general allergic reaction occurs, stop use and seek medical help right away.

Sore throat warning:If sore throat is severe, persists for more than 2 days, is accompanied or followed by fever, headache, rash, nausea, or vomiting, consult a doctor promptly.

Do not use

- with any other drug containing acetaminophen (prescription or nonprescription). If you are not sure whether a drug contains acetaminophen, ask a doctor or pharmacist.
- if you are now taking a prescription monoamine oxidase inhibitor (MAOI) (certain drugs for depression, psychiatric, or emotional conditions, or Parkinson's disease), or for 2 weeks after stopping the MAOI drug. If you do not know if your prescription drug contains an MAOI, ask a doctor or pharmacist before taking this product.
- if you have ever had an allergic reaction to this product or any of its ingredients
- in children under 12 years of age

Ask a doctor before use if you have

- liver disease
- persistent or chronic cough such as occurs with smoking, asthma or emphysema
- cough that is accompanied with excessive phlegm (mucus)
- a sodium-restricted diet

Ask a doctor or pharmacist before use if you aretaking the blood thinning drug warfarin

Stop use and ask a doctor if

- pain or cough gets worse or lasts more than 7 days
- fever gets worse or lasts more than 3 days
- redness or swelling is present
- new symptoms occur
- cough comes back or occurs with rash or headache that lasts. These could be signs of a serious condition.

PREGNANCY OR BREAST FEEDING

If pregnant or breast-feeding,ask a health professional before use.

Keep out of reach of children.In case of overdose, get medical help or contact a Poison Control Center right away. Quick medical attention is critical for adults as well as for children even if you do not notice any signs or symptoms.

Directions

- do not take more than recommended dose
- adults and children 12 years and over: take 30 mL in the dosing cup provided every 4 hours. Do not exceed 150 mL (5 doses) in 24 hours or as directed by a doctor.
- children under 12 years of age: do not use

Other information
• each 30 mL contains: sodium 38 mg
• store between 20º to 25ºC (68º to 77ºF)

Inactive ingredients

anhydrous citric acid, Edetate Disodium, FD&C blue #1, FD&C red # 40, flavor, glycerin, Poloxamer, propylene glycol, purified water, Sodium benzoate, potassium Citrate, sorbitol liquid, xanthan gum

Questions or comments?1-866-467-2748

PACKAGE LABEL

Walgreens

Compare to the active ingredients in Coricidin® HBP Maximum Strength††

NDC# 0363-8100-12

Cold, Cough & Flu Relief

ACETAMINOPHEN 650 mg /PAIN RELIEVER/FEVER REDUCER

DEXTROMETHORPHAN HBr 20 mg /COUGH SUPPRESSANT

Maximum Strength

- For relief of sore throat, fever, headache, cough, body aches & pains
- Cold relief for people with high blood pressure*
- sugar free
- Alcohol Free

Natural Cherry flavor

*Decongestant free

Maximum Strength per 4-hour dose

12 FL OZ (355 mL)

†Our pharmacist recommend the Walgreens brand. We invite you to compare to national brands.

††This product is not manufactured or distributed by Bayer Healthcare LLC, owner of the registered trademark Coricidin® HBP.

DISTRIBUTED BT: WALGREEN CO.,

DEERFIELD, IL 60015

100% SATISFACTION GUARANTEED

Walgreens.com

©2025 Walgreen Co.

MADE IN THE U.S.A. WITH DOMESTIC AND IMPORTED INGREDIENTS